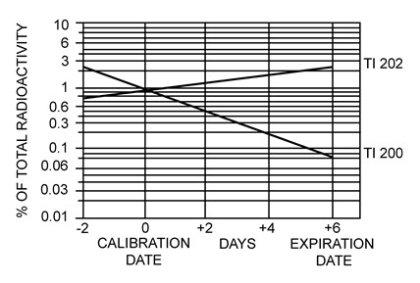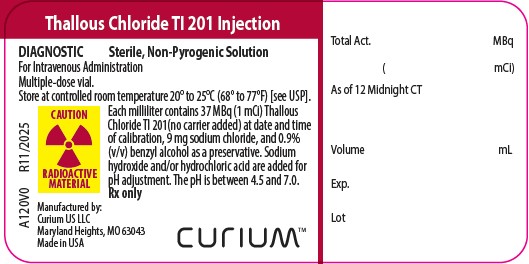 DRUG LABEL: THALLOUS CHLORIDE Tl 201
NDC: 69945-120 | Form: INJECTION, SOLUTION
Manufacturer: Curium US LLC
Category: prescription | Type: HUMAN PRESCRIPTION DRUG LABEL
Date: 20251222

ACTIVE INGREDIENTS: THALLOUS CHLORIDE TL-201 1 mCi/1 mL
INACTIVE INGREDIENTS: SODIUM CHLORIDE; BENZYL ALCOHOL; HYDROCHLORIC ACID; SODIUM HYDROXIDE

HIGHLIGHTS OF PRESCRIBING INFORMATION

These highlights do not include all the information needed to use THALLOUS CHLORIDE Tl 201 INJECTION safely and effectively. See full prescribing information for THALLOUS CHLORIDE Tl 201 INJECTION.
THALLOUS CHLORIDE Tl 201 injection, for intravenous use
Initial U.S. Approval: 1977

1 INDICATIONS AND USAGE

Thallous Chloride Tl 201 Injection is a radioactive diagnostic drug indicated for use with planar scintigraphy or single-photon emission computed tomography (SPECT) for:

- Myocardial perfusion imaging in adults for the diagnosis of coronary artery disease by localization of:
  - Non-reversible defects (myocardial infarction)
  - Reversible defects (myocardial ischemia) when used in conjunction with exercise or pharmacologic stress
- Localization of sites of parathyroid hyperactivity pre- and post-operatively in adults with elevated serum calcium and parathyroid hormone levels (1)

2 DOSAGE AND ADMINISTRATION

- • For myocardial perfusion imaging:
  - Planar 37 MBq to 74 MBq (1 mCi to 2 mCi) (2.2)
  - SPECT 74 MBq to 111 MBq (2 mCi to 3 mCi) (2.2)
- For localization of parathyroid hyperactivity, planar or SPECT: 75 MBq to 130 MBq (2 mCi to 3.5 mCi)
- Administer by intravenous injection. (2.2)
- See full prescribing information for administration and imaging instructions and radiation dosimetry information. (2.3, 2.4)

3 DOSAGE FORMS AND STRENGTHS

Injection: available in the following strength at calibration time in a multiple-dose vial

- 207.2 MBq (5.6 mCi) per 5.6 mL (37 MBq (1 mCi) per mL) (3)

4 CONTRAINDICATIONS

None

5 WARNINGS AND PRECAUTIONS

- Hypersensitivity Reactions: Anaphylactic reactions characterized by cardiovascular, respiratory, and cutaneous symptoms may occur. Have resuscitation equipment and trained staff readily available. (5.1)
- Risk Associated with Stress Testing: Induction of cardiovascular stress may be associated with serious adverse reactions. Perform stress testing in a setting where cardiac resuscitation equipment and trained staff are readily available. (5.2)
- Radiation Risk: Ensure safe handling to minimize radiation exposure to patients and health care providers. (2.1, 5.3)

6 ADVERSE REACTIONS

The following adverse reactions have been reported. In patients who have undergone stress testing: myocardial infarction, arrhythmia, hypotension, bronchoconstriction, and cerebrovascular events. Adverse reactions in other patients: nausea, vomiting, diarrhea, injection site reactions, chills, fever, sweating, hypersensitivity (anaphylaxis, hypotension, shortness of breath, pruritus, flushing, diffuse rash). (6)

To report SUSPECTED ADVERSE REACTIONS, contact Curium US LLC at 1-866-789-2211 or FDA at 1-800-FDA-1088 or www.fda.gov/medwatch.

8 USE IN SPECIFIC POPULATIONS

Lactation: Temporarily discontinue breastfeeding. A lactating woman should pump and discard breast milk for at least 96 hours after Thallous Chloride Tl 201 Injection administration. (8.2)

FULL PRESCRIBING INFORMATION

1 INDICATIONS AND USAGE

Thallous Chloride Tl 201 Injection is indicated for use with planar scintigraphy or single-photon emission computed tomography (SPECT) for the following applications:

- Myocardial perfusion imaging in adults for the diagnosis of coronary artery disease by localization of:
  - Non-reversible defects (myocardial infarction)
  - Reversible defects (myocardial ischemia) when used in conjunction with exercise or pharmacologic stress
- Localization of sites of parathyroid hyperactivity pre- and post-operatively in adults with elevated serum calcium and parathyroid hormone levels

2 DOSAGE AND ADMINISTRATION

2.1 Radiation Safety – Drug Handling

Handle Thallous Chloride Tl 201 Injection with appropriate safety measures to minimize radiation exposure [see Warnings and Precautions (5.3)] . Use waterproof gloves, effective radiation shielding, and other appropriate safety measures when preparing and handling Thallous Chloride Tl 201 Injection.

Radiopharmaceuticals should be used by or under the control of healthcare providers who are qualified by specific training and experience in the safe use and handling of radionuclides, and whose experience and training have been approved by the appropriate governmental agency authorized to license the use of radionuclides.

2.2 Recommended Dose

Myocardial Perfusion Imaging in Adults

- Planar scintigraphy: 37 MBq to 74 MBq (1 mCi to 2 mCi) administered intravenously
- SPECT: 74 MBq to 111 MBq (2 mCi to 3 mCi) administered intravenously

Parathyroid Hyperactivity Localization in Adults

Planar or SPECT: 75 MBq to 130 MBq (2 mCi to 3.5 mCi) administered intravenously

2.3 Administration and Imaging Instructions

Patient Preparation
Instruct patients to hydrate before and after Thallous Chloride Tl 201 Injection administration and to void before imaging and frequently thereafter following Thallous Chloride Tl 201 Injection administration [see Warnings and Precautions (5.3)] .

Administration

- Use aseptic technique and radiation shielding when withdrawing and administering Thallous Chloride Tl 201 Injection.
- Visually inspect the drug for particulate matter and discoloration prior to administration, whenever the solution and container permit. Do not use if contents are turbid or discolored.
- Measure the patient dose with a dose calibrator immediately prior to administration.
- Use within 6 days from the manufacturer’s calibration date or 9 days from the date of manufacture, whichever comes first.
- Dispose of unused products in a safe manner in compliance with applicable regulations.

Myocardial Perfusion Imaging
For resting myocardial studies, begin imaging 10 minutes to 20 minutes after administration of Thallous Chloride Tl 201 Injection. Target-to-background ratios are improved when patients are injected upright and in the fasting state; the upright position reduces the hepatic and gastric thallium-201 concentration.

For exercise stress testing, administer Thallous Chloride Tl 201 Injection at the start of a period of maximum stress, which is sustained for approximately 30 seconds after injection. Begin imaging within 10 minutes after administration to obtain maximum target-to-background ratios. Within 2 hours after the completion of the stress testing, the target-to-background ratios may decrease in lesions that are attributable to transient ischemia.

Parathyroid Hyperactivity Localization
For localization of parathyroid hyperactivity, administer Thallous Chloride Tl 201 Injection before, with, or after a minimal dose of a thyroid imaging agent such as sodium pertechnetate Tc 99m injection or sodium iodide I 123 capsules to enable thyroid subtraction imaging.

2.4 Radiation Dosimetry

Estimated absorbed radiation doses from an intravenous injection of Thallous Chloride Tl 201 Injection are shown in Table 1.

Table 1. Estimated Absorbed Radiation Dose per Injected Activity in Organs and Tissues of Adults from Intravenous Administration of Thallous Chloride Tl 201 Injection^1
Organ/ Tissue | Absorbed Dose per Unit Activity Administered (mGy/MBq)
Adrenals | 0.063
Brain | 0.057
Breasts | 0.034
GB Wall | 0.083
GI Tract
LLI Wall | 0.300
Small Intestine | 0.379
Stomach | 0.171
ULI Wall | 0.297
Heart Wall | 0.247
Kidneys | 0.410
Liver | 0.094
Lungs | 0.047
Muscle | 0.046
Ovaries | 0.102
Pancreas | 0.075
Red Marrow | 0.044
Bone Surfaces | 0.094
Skin | 0.032
Spleen | 0.166
Testes | 0.209
Thymus | 0.046
Thyroid | 0.542
Urinary Bladder Wall | 0.063
Uterus | 0.086
Total Body | 0.058
Effective Dose (mSv/MBq) | 0.145

^1Assumed percentage of 98.3% thallium-201, 0.3% thallium-200, 1.2% thallium-202, and 0.2% lead-203

3 DOSAGE FORMS AND STRENGTHS

Injection: a clear, colorless solution available in the following strength at calibration time:

- 207.2 MBq (5.6 mCi) per 5.6 mL (37 MBq (1 mCi) per mL) in a multiple-dose vial

4 CONTRAINDICATIONS

None.

5 WARNINGS AND PRECAUTIONS

5.1 Hypersensitivity Reactions

Thallous Chloride Tl 201 Injection may cause anaphylactic reactions characterized by cardiovascular, respiratory, and cutaneous symptoms [see Adverse Reactions (6)] . Have resuscitation equipment and trained staff readily available.

5.2 Risks Associated with Stress Testing

Induction of cardiovascular stress might be associated with serious adverse reactions such as myocardial infarction, arrhythmia, hypotension or hypertension, ECG abnormalities, chest pain, bronchoconstriction, and cerebrovascular events [see Adverse Reactions (6)] . Perform stress testing in the setting where cardiac resuscitation equipment and trained staff are readily available. Perform pharmacologic stress in accordance with the pharmacologic stress agent’s prescribing information.

5.3 Radiation Risk

Thallous Chloride Tl 201 Injection contributes to a patient's overall long-term cumulative radiation exposure. Long-term cumulative radiation exposure is associated with an increased risk of cancer. Ensure safe handling to minimize radiation exposure to patients and health care providers. Advise patients to hydrate before and after administration and to void frequently after administration [see Dosage and Administration (2.1, 2.3)].

5.4 Injection Site Reactions and Tissue Damage

Injection site reactions and extravasation have been reported after administration of Thallous Chloride Tl 201 Injection [see Adverse Reactions (6)] . Administer Thallous Chloride Tl 201 Injection strictly into the vein to avoid local tissue accumulation and irradiation. Confirm intravenous patency before injection.

6 ADVERSE REACTIONS

The following clinically significant adverse reactions are described elsewhere in the labeling:

- Hypersensitivity Reactions [see Warnings and Precautions (5.1)]
- Risk Associated with Stress Testing [see Warnings and Precautions (5.2)]
- Injection Site Reactions and Tissue Damage [see Warnings and Precautions (5.4)]

The following adverse reactions associated with the use of Thallous Chloride Tl 201 Injection were identified in clinical studies or postmarketing reports. Because some of these reactions were reported voluntarily from a population of uncertain size, it is not always possible to reliably estimate their frequency or establish a causal relationship to drug exposure:

Cardiovascular, respiratory, and cerebrovascular disorders:myocardial infarction, arrhythmia, hypotension, bronchoconstriction, and cerebrovascular events in patients who have undergone stress testing

Gastrointestinal disorders:nausea, vomiting, and diarrhea

General disorders and administration site conditions:injection site reactions (burning, pain, redness, swelling, warmth, and tissue damage with chronic ulcer formation), chills, fever, and sweating

Immune system disorders:hypersensitivity (anaphylaxis, hypotension, shortness of breath, pruritus, flushing, and diffuse rash)

8 USE IN SPECIFIC POPULATIONS

8.1 Pregnancy

Risk Summary

There are no data on Thallous Chloride Tl 201 Injection use in pregnant women to evaluate for a drug-associated risk of major birth defects, miscarriage, or adverse maternal or fetal outcomes. Studies using human placentas demonstrate that thallous chloride Tl 201 crosses the placenta. No animal reproductive studies have been conducted.

All radiopharmaceuticals, including Thallous Chloride Tl 201 Injection have the potential to cause fetal harm depending on the fetal stage of development and the magnitude of the radiation dose. If considering administration of Thallous Chloride Tl 201 Injection to a pregnant woman, inform the patient about the potential for adverse pregnancy outcomes based on the radiation dose from Thallous Chloride Tl 201 Injection and gestational timing of exposure.

The background risk of major birth defects and miscarriage for the indicated population is unknown. All pregnancies have a background risk of birth defects, loss, or other adverse outcomes. In the U.S. general population, the estimated background risk of major birth defects and miscarriage in clinically recognized pregnancies is 3% and 10% to 20%, respectively.

8.2 Lactation

Risk Summary

Thallous chloride Tl 201 has been detected in the milk of lactating women. There are no data on the effects of thallous chloride Tl 201 on milk production or the effects of thallous chloride Tl 201 on the breastfed infant.

Exposure of the breastfed infant to thallous chloride Tl 201 can be minimized by advising a lactating woman to temporarily discontinue breastfeeding and pump and discard milk for a minimum of 96 hours after administration of Thallous Chloride Tl 201 Injection. Minimize close contact with infants if the administered dose would result in an effective dose greater than 1 mSv to the infant. The developmental and health benefits of breastfeeding should be considered along with the mother’s clinical need for Thallous Chloride Tl 201 Injection and any potential adverse effects on the breastfed infant from Thallous Chloride Tl 201 Injection or from the underlying maternal condition.

8.4 Pediatric Use

The safety and effectiveness of Thallous Chloride Tl 201 Injection in pediatric patients have not been established.

8.5 Geriatric Use

Clinical studies of Thallous Chloride Tl 201 Injection for myocardial perfusion imaging did not include sufficient numbers of subjects aged younger than 65 years to determine whether they respond differently from younger subjects. Other reported experience has not revealed clinically relevant differences in the response of elderly in comparison to younger patients.

This drug is known to be substantially excreted by the kidney, and the risk of toxic reactions to this drug may be greater in patients with impaired renal function. Because elderly patients are more likely to have decreased renal function, care should be taken in dose selection, and it may be useful to monitor renal function.

10 OVERDOSAGE

In the event of the administration of an overdose of Thallous Chloride Tl 201 Injection, the absorbed dose to the patient should be reduced where possible by increasing the excretion of the radionuclide by forced diuresis with frequent voiding and stimulation of peristalsis.

11 DESCRIPTION

11.1 Drug Characteristics

Thallous Chloride Tl 201 Injection is a sterile, radioactive diagnostic drug for intravenous use.

Each mL contains 37 MBq (1 mCi) thallous chloride Tl 201 at calibration time and the following inactive ingredients: 9 mg sodium chloride and 0.9% (v/v) benzyl alcohol. The pH is adjusted to between 4.5 to 7.0 with hydrochloric acid and/or sodium hydroxide.

Thallium-201 is cyclotron produced. At the time of calibration it contains no more than 1% thallium-200, no more than 1% thallium-202, no more than 0.25% lead-203, and no less than 98% thallium-201 as a percentage of total activity. No carrier has been added.

The concentration of each radionuclidic contaminant changes with time. Figure 1 shows maximum concentration of thallium-200 (Tl 200) and thallium-202 (Tl 202) radionuclidic contaminants as a function of time.

Figure 1. Radionuclidic Contaminants

11.2 Nuclear Physical Characteristics

Thallium-201, with a physical half-life of 72.9 hours, decays by electron capture to mercury-201. Photons that are useful for detection and imaging are listed in Table 2. The lower energy x-rays obtained from the mercury-201 daughter of thallium-201 are recommended for myocardial imaging, because the mean percent disintegration at 68.9 to 80.3 keV is much greater than the combination of gamma-4 and gamma-6 mean percent disintegration.

Table 2. Principal Radiation Emission Data
Radiation | Mean Percent/ Disintegration | Energy (keV)
Gamma-4 | 2.7 | 135.3
Gamma-6 | 10.0 | 167.4
Mercury; x-rays | 94.4 | 68.9-80.3

The specific gamma ray constant for thallium-201 is 0.45 R/mCi-hr at 1 cm. The first half-value thickness of lead (Pb) is 0.026 cm. A range of values for the relative attenuation of the radiation emitted by this radionuclide that results from interposition of various thicknesses of Pb is shown in Table 3. For example, the use of 0.194 cm of lead will decrease the external radiation exposure by a factor of about 1,000.

Table 3. Radiation Attenuation by Lead Shielding
cm of; Lead (Pb) | Coefficient of; Attenuation
0.026 | 0.5
0.052 | 10^-1
0.089 | 10^-2
0.194 | 10^-3
0.310 | 10^-4

To correct for physical decay of the radionuclide, the fractions that remain at selected intervals after calibration time are shown in Table 4.

Table 4. Physical Decay Chart for Thallium-201; Half-Life 72.9 Hours
Hours | Fraction Remaining | Hours | Fraction Remaining
0* | 1 | 66 | 0.53
6 | 0.95 | 72 | 0.50
12 | 0.89 | 78 | 0.48
18 | 0.84 | 84 | 0.45
24 | 0.80 | 90 | 0.43
30 | 0.75 | 96 | 0.40
36 | 0.74 | 108 | 0.36
42 | 0.67 | 120 | 0.32
48 | 0.63 | 132 | 0.29
54 | 0.60 | 144 | 0.25
60 | 0.57

* Calibration Time

12 CLINICAL PHARMACOLOGY

12.1 Mechanism of Action

Thallous chloride Tl 201 with no carrier added accumulates in viable myocardium in a manner analogous to that of potassium. Experiments in healthy subjects using labeled microspheres have shown that the myocardial distribution of thallous chloride Tl 201 correlates with regional perfusion.

In clinical studies, Thallous Chloride Tl 201 images have been found to visualize areas of infarction as “cold” or nonlabeled regions that were confirmed by electrocardiographic and enzyme changes. Regions of transient myocardial ischemia corresponding to areas perfused by coronary arteries with partial stenoses have been visualized when Thallous Chloride Tl 201 Injection was administered in conjunction with an exercise stress test. Anatomic configurations may interfere with visualization of the right coronary artery territory.

12.2 Pharmacodynamics

The pharmacodynamics of thallous chloride Tl 201 have not been established.

12.3 Pharmacokinetics

Distribution
After intravenous administration, thallous chloride Tl 201 clears from the blood with maximal concentration in normal myocardium occurring at about 10 minutes. It will, in addition, localize in parathyroid adenomas; it is not specific since it will localize to a lesser extent in sites of parathyroid hyperplasia and other abnormal tissues such as thyroid adenoma, neoplasia (e.g., parathyroid carcinoma), and sarcoid. Biodistribution is generally proportional to organ blood flow at the time of injection. Blood clearance of thallous chloride Tl 201 is primarily by the myocardium, thyroid, liver, kidneys, and stomach with the remainder distributing fairly uniformly throughout the body. The dosimetry data in Table 1 reflect this distribution pattern and are based on a biological half-life of 2.4 days.

Elimination
Five minutes after intravenous administration only 5% to 8% of injected activity remained in the blood. A biexponential disappearance curve was obtained, with 91.5 % of the blood radioactivity disappearing with a half-time of about 5 minutes. The remainder had a half-time of about 40 hours.

Excretion
Approximately 4% to 8% of the injected dose was excreted in the urine in the first 24 hours. The whole body disappearance half-time was 9.8 ± 2.5 days. Kidney concentration was found to be about 3% of the injected activity and the testicular content was 0.15%. Net thyroid activity was determined to be only 0.2% of the injected dose, and the activity disappeared in 24 hours. From anterior and posterior whole-body scans, it was determined that about 45% of the injected dose was in the large intestines and contiguous structures (liver, kidneys, abdominal musculature).

13 NONCLINICAL TOXICOLOGY

13.1 Carcinogenesis, Mutagenesis, Impairment of Fertility

No long-term animal studies have been performed to evaluate carcinogenic potential, mutagenic potential, or whether this drug affects fertility in males or females.

16 HOW SUPPLIED/STORAGE AND HANDLING

How Supplied
Thallous Chloride Tl 201 Injection is supplied as a clear, colorless solution in the following strength at calibration time:

207.2 MBq (5.6 mCi) per 5.6 mL (37 MBq (1 mCi) per mL) in a multiple-dose vial (NDC 69945-120-56)

Storage and Handling

Store Thallous Chloride Tl 201 Injection in the original container with radiation shielding at 20°C to 25°C (68°F to 77°F) [see USP Controlled Room Temperature].

Dispose of any unused product in accordance with all federal, state, and local laws and institutional requirements.

This preparation is for use by persons under license by the Nuclear Regulatory Commission or the relevant regulatory authority of an Agreement State.

17 PATIENT COUNSELING INFORMATION

Radiation Risk
Advise patients of the radiation risk of Thallous Chloride Tl 201 Injection. Instruct patients to drink water to ensure adequate hydration prior to administration of Thallous Chloride Tl 201 Injection and to continue drinking and voiding frequently following administration to reduce radiation exposure [see Warnings and Precautions (5.3)] .

Pregnancy
Inform pregnant women of the risk of fetal exposure to radiation dose if they undergo an imaging procedure with Thallous Chloride Tl 201 Injection [see Use in Specific Populations (8.1)] .

Lactation
Advise a lactating woman to temporarily discontinue breastfeeding and to pump and discard breastmilk for at least 96 hours after administration of Thallous Chloride Tl 201 Injection to minimize radiation exposure to a breastfed infant [see Use in Specific Populations (8.2)] .

Manufactured by:

Curium US LLC
Maryland Heights, MO 63043

Made in USA

©2025 Curium US LLC. CuriumTMand the Curium logo are trademarks of a Curium company.

A120I0

CURIUM™

PRINCIPAL DISPLAY PANEL

Thallous Chlloride TI 201 Injection
DIAGNOSTIC Sterile, Non-Pyrogenic Solution For Intravenous Administration

Multiple-dose vial

Store at Controlled Room Temperature 20 ºto 25ºC (68 ºto 77ºF) [see USP]. Each milliliter contains 37 MBq (1 mCi) Thallous Chloride TI 201 (no carrier added) at date and time of calibration, 9 mg sodium chloride, and 0.9% (v/v) benzyl alcohol as a preservative. Sodium hydroxide and/or hydrochloric acid are added for pH adjustment. The pH is between 4.5 and 7.0.

Rx only
CAUTION RADIOACTIVE MATERIAL

Manufactured by:
Curium US LLC
Maryland Heights, MO 63043

Made in USA
CURIUM™

A120V0 R11/2025